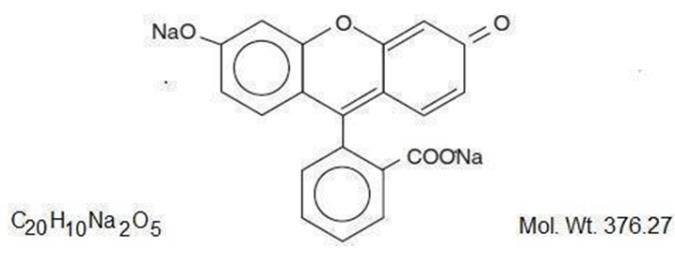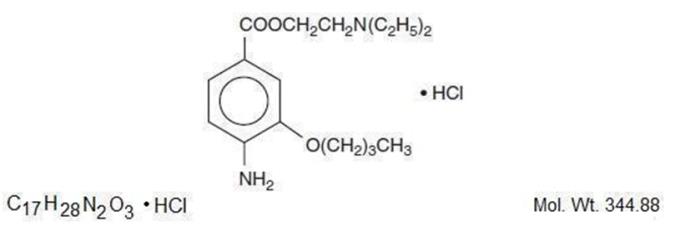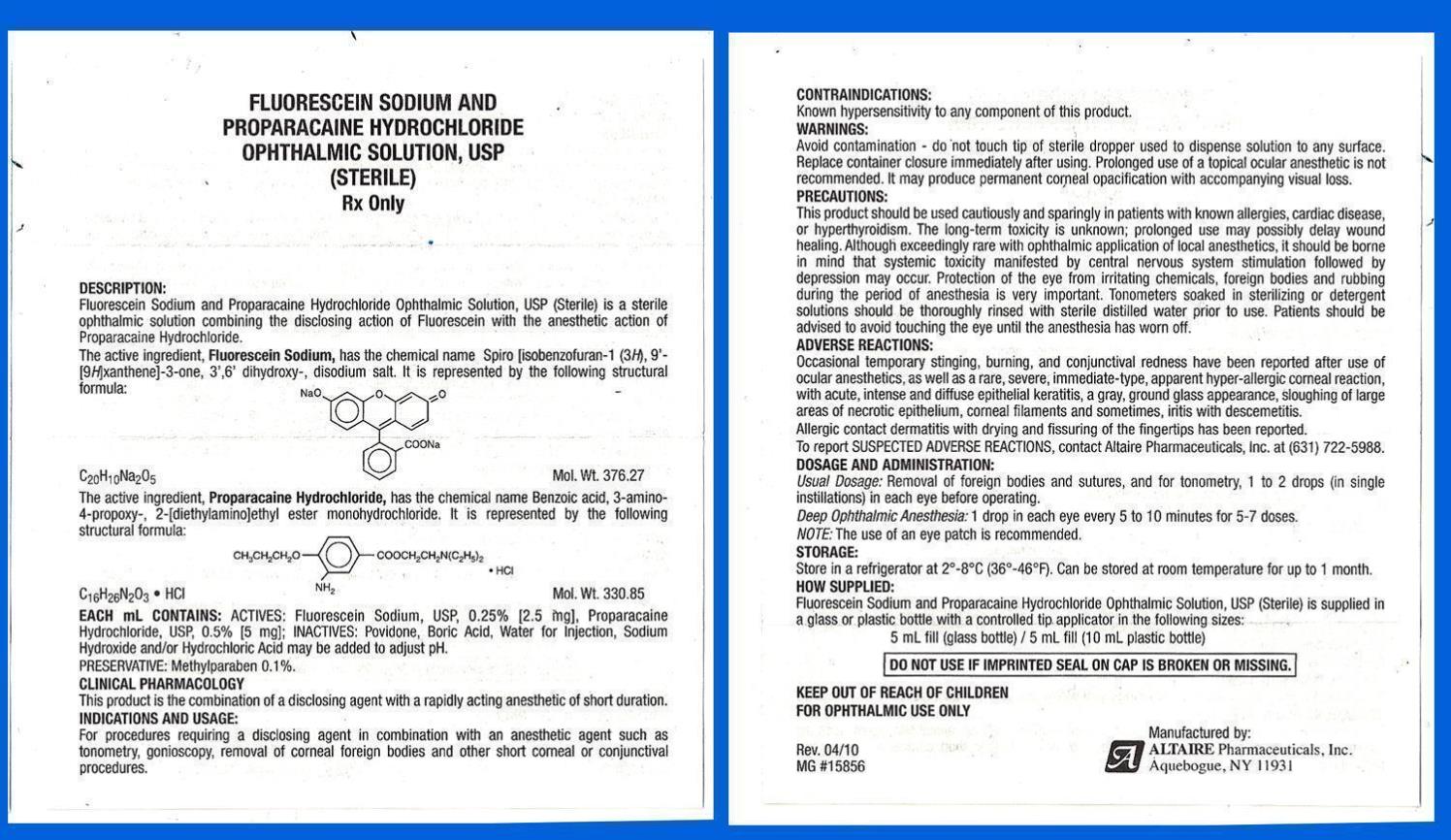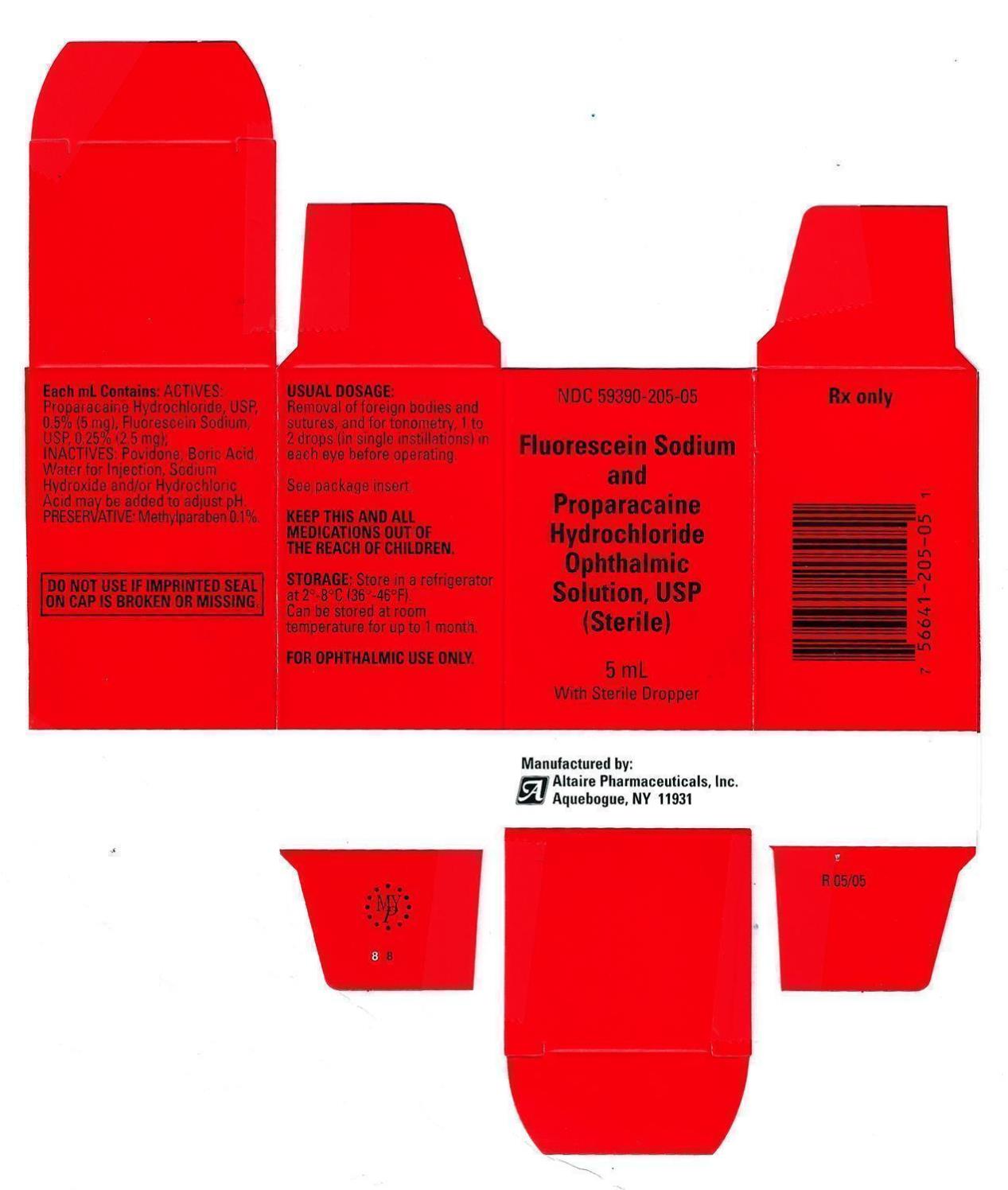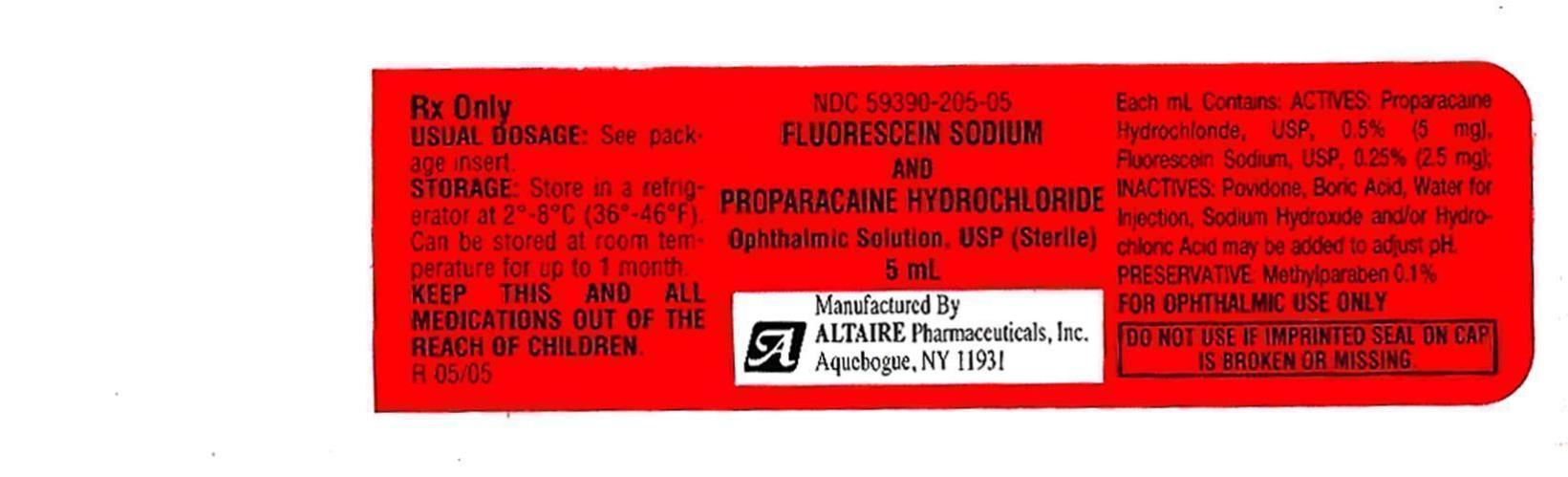 DRUG LABEL: Fluorescein Sodium and Proparacaine Hydrochloride
NDC: 59390-205 | Form: SOLUTION/ DROPS
Manufacturer: Altaire Pharmaceuticals Inc.
Category: prescription | Type: HUMAN PRESCRIPTION DRUG LABEL
Date: 20221028

ACTIVE INGREDIENTS: FLUORESCEIN SODIUM 2.5 mg/1 mL; PROPARACAINE HYDROCHLORIDE 5 mg/1 mL
INACTIVE INGREDIENTS: POVIDONE; BORIC ACID; WATER; SODIUM HYDROXIDE; HYDROCHLORIC ACID; METHYLPARABEN

Fluorecein Sodium and Proparacaine Hydrochloride Opthahalmic Solution, USP

Fluorescein Sodium and Proparacaine Hydrochloride Ophthalmic Solution, USP

DESCRIPTION:

Fluorescein Sodium and Proparacaine Hydrochloride Ophthalmic Solution, USP (Sterile) is a sterile ophthalmic solution combining the disclosing action of Fluorescein with the anesthetic action of Proparacaine Hydrochloride.

The active ingredient, Fluorescein Sodium, has the chemical name Spiro [isobenzofuran-1 (3H), 9'-[9H]xanthene]-3-one, 3' ,6' dihydroxy-,disodium salt. It is represented by the following structural formula:

The active ingredient, Proparacaine Hydrochloride, has the chemical name Benzoic acid, 3-amino-4-propoxy-, 2-[diethylamino]ethyl ester monohydrochloride. It is represented by the following structural formula:

EACH mL CONTAINS: ACTIVES: Fluorescein Sodium, USP, 0.25% [2.5 mg]. Proparacaine Hydrochloride, USP, 0.5% [5mg]; INACTIVES: Povidone, Boric Acid, Water for Injection, Sodium Hydroxide, or/and Hydrochloric Acid may be added to adjust pH.
PRESERVATIVE: Methylparaben 0.1%.

CLINICAL PHARMACOLOGY

This product is the combination of a disclosing agent with a rapidly acting anesthetic of short duration.
For procedures requiring a disclosing agent in combination with an anesthetic agent such as tonometry, gonioscopy, removal of corneal foreign bodies and other short corneal or conjunctival procedures.

CONTRAINDICATIONS:

Known hypersensitivity to any component of this product.

WARNINGS:

Avoid contamination - do not touch tip of sterile dropper used to dispense solution to any surface. Replace container closure immediately after using. Prolonged use of a topical ocular anesthetic is not recommended. It may product permanent corneal opacification with accompanying visual loss.

PRECAUTIONS:

This product should be used cautiously and sparingly in patients with known allergies, cardiac disease, or hyperthyroidism. The long-term toxicity is unknown; prolonged use may possibly delay wound healing. Although exceedingly rare with ophthalmic application of local anesthetics, it should be borne in mind that systemic toxicity manifested by central nervous system stimulation followed by depression may occur. Protection of the eye from irritating chemicals, foreign bodies and rubbing during the period of anesthesia is very important. Tonometers soaked in sterilizing or detergent solutions should be thoroughly rinsed with sterile distilled water prior to use. Patients should be advised to avoid touching the eye until the anesthesia has worn off.

ADVERSE REACTIONS:

Occasional temporary stinging, burning, and conjunctival redness have been reported after use of ocular anesthetics, as well as a rare, severe, immediate-type, apparent hyper-allergic corneal reaction, with acute, intense and diffuse epithelial keratitis, a gray, ground glass appearance, sloughing of large areas of necrotic epithelium, corneal filaments and sometimes, iritis with descementitis. Allergic contact dermatitis with drying and fissuring of the fingertips has been reported.

To report SUSPECTED ADVERSE REACTIONS, contact Altaire Pharmaceuticals, Inc. at (631) 722-5988.

DOSAGE AND ADMINISTRATION:

Usual Dosage: Removal of foreign bodies and sutures, and for tonometry, 1 to 2 drops (in single instillations) in each eye before operating.
Deep Ophthalmic Anesthesia: 1 drop in each eye every 5 to 10 minutes for 5-7 doses.

NOTE: The use of an eye patch is recommended.

STORAGE:

Store in refrigerator at 2°-8°C (36°-46°F). Can be stored at room temperature for up to 1 month.

HOW SUPPLIED:

Fluorescein Sodium and Proparacaine Hydrochloride Ophthalmic Solution, USP (Sterile) is supplied in a glass or plastic bottle with a controlled tip applicator in the following sizes:
5 mL fill (glass bottle) with dropper

DO NOT USE IS IMPRINTED SEAL ON CAP IS BROKEN OR MISSING.

KEEP OUT OF REACH OF CHILDREN

FOR OPHTHALMIC USE ONLY

Manufactured By:
Altaire Phamacueticals, Inc.
311 West Lane
Aquebogue, NY 119311

Tel: 631-722-5988

Principal Display Panel

Fluorescein Sodium and
Proparacaine Hydrochloride
Ophthalmic Solutions, USP
(STERILE)
Rx Only

5 mL